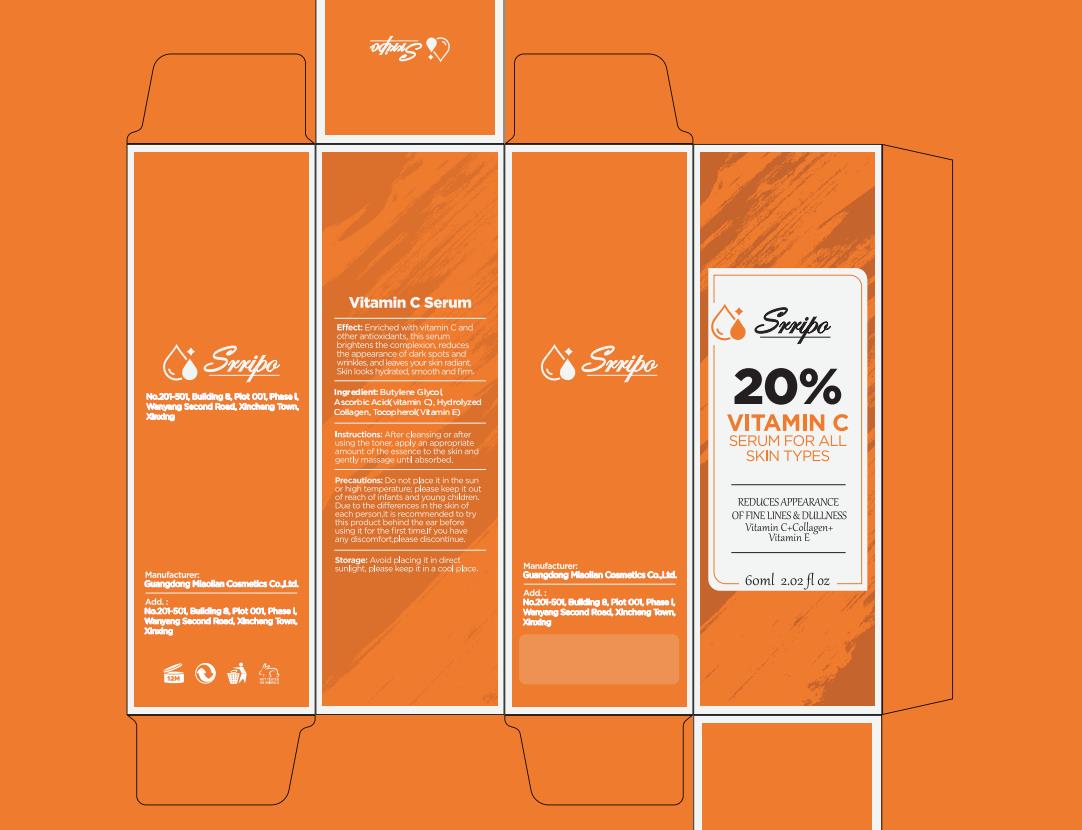 DRUG LABEL: Srripo 20% VITAMIN C SERUM
NDC: 84507-029 | Form: LIQUID
Manufacturer: Guangdong Miaolian Cosmetics Co., Ltd.
Category: otc | Type: HUMAN OTC DRUG LABEL
Date: 20250210

ACTIVE INGREDIENTS: ASCORBIC ACID 20 mg/100 mL
INACTIVE INGREDIENTS: BUTYLENE GLYCOL; TOCOPHEROL; EQUUS CABALLUS COLLAGEN

DOSAGE AND ADMINISTRATION

After cleansing or afterusing the toner, apply an appropriateamount of the essence to the skin andgently massage until absorbed.

WARNINGS

Forevemaluseony Avoid coniac wth eves li coniac ocus nse ihorouthly wt waier

Keep out ofreach oi chidrenifvou ale preanant.nursing.

Consutyou healthcare provider before using the product

INACTIVE INGREDIENT

BUTYLENE GLYCOL

INDICATIONS AND USAGE

Do not place it in the sunor high temperature, please keep it outof reach of infants and young children.

Due to the differences in the skin ofeach person,it is recommended to trythis product behind the ear beforeusing it for the first time.

lf you haveany discomfort,please discontinue.
Avoid placing it in directsunlight, please keep it in a cool place.

KEEP OUT OF REACH OF CHILDREN

Please keep it outof reach of infants and young children.

PURPOSE

Enriched with vitamin C andother antioxidants, this serumbrightens the complexion, reducesthe appearance of dark spots andwrinkles, and leaves your skin radiant.Skin looks hydrated, smooth and firm.

ACTIVE INGREDIENT

20% ASCORBIC ACID